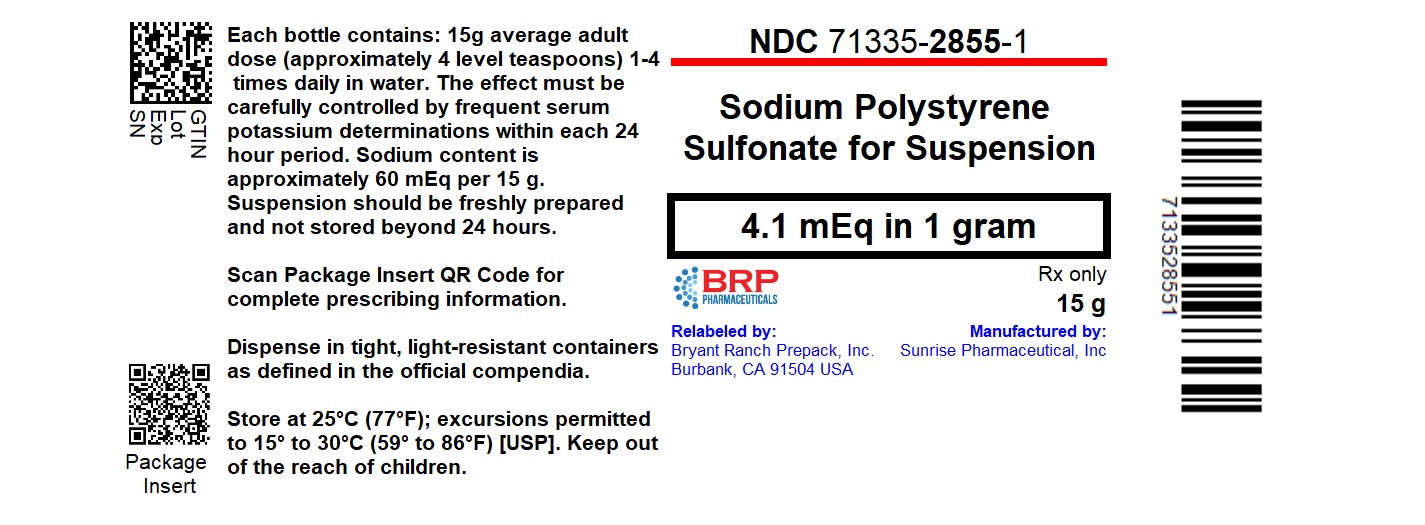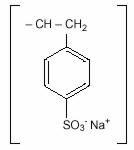 DRUG LABEL: SODIUM POLYSTYRENE SULFONATE
NDC: 71335-2855 | Form: POWDER, FOR SUSPENSION
Manufacturer: Bryant Ranch Prepack
Category: prescription | Type: HUMAN PRESCRIPTION DRUG LABEL
Date: 20251021

ACTIVE INGREDIENTS: SODIUM POLYSTYRENE SULFONATE 4.1 meq/1 g

HIGHLIGHTS OF PRESCRIBING INFORMATION

These highlights do not include all the information needed to use sodium polystyrene sulfonate for suspension safely and effectively. See full prescribing information for sodium polystyrene sulfonate for suspension.
Sodium polystyrene sulfonate for suspension, for oral or rectal use
Initial U.S. Approval: 1958

1 INDICATIONS AND USAGE

Sodium polystyrene sulfonate for suspension is a potassium binder indicated for the treatment of hyperkalemia (1).

Limitation of Use:

Sodium polystyrene sulfonate for suspension should not be used an emergency treatment for life threatening hyperkalemia because of its delayed onset of action (1).

2 DOSAGE AND ADMINISTRATION

Oral: The average total daily adult dose of sodium polystyrene sulfonate is 15 g to 60 g, administered as a 15-g dose (four level teaspoons), one to four times daily (2.1).

Rectal: The average adult dose is 30 g to 50 g every six hours (2.1).

3 DOSAGE FORMS AND STRENGTHS

Sodium polystyrene sulfonate for suspension is available as a golden brown, finely ground
powder (3)

4 CONTRAINDICATIONS

- Hypersensitivity to polystyrene sulfonate resins (4)
- Obstructive bowel disease (4)
- Neonates with reduced gut motility (4)

5 WARNINGS AND PRECAUTIONS

- Intestinal Necrosis: cases of intestinal necrosis and other serious gastrointestinal events have been reported (5.1).
- Electrolyte Disturbances: Severe hypokalemia can occur. (5.2).
- Fluid overload in patient sensitive to high sodium intake: Monitor patients who are sensitive to sodium intake for signs of fluid overload. (5.3).
- Risk of aspiration: Acute bronchitis or bronchopneumonia caused by inhalation of sodium polystyrene sulfonate particles has been reported. (5.4).

6 ADVERSE REACTIONS

Adverse reactions reported include: anorexia, constipation, diarrhea, fecal impaction, gastrointestinal concretions (bezoars), ischemic colitis, nausea, vomiting (6).

To report SUSPECTED ADVERSE REACTIONS, contact Sunrise Pharmaceutical Inc. at 1-732-382-6085 or FDA at 1-800-FDA-1088 or www.fda.gov/medwatch.

7 DRUG INTERACTIONS

- Take other orally administered drugs at least 3 hours before or 3 hours after sodium polystyrene sulfonate (7.1).
- Cation-Donating Antacids: may reduce the resin’s potassium exchange capability and increase risk of systemic alkalosis (7.2).
- Sorbitol: Concomitant use may contribute to the risk of intestinal necrosis and is not recommended (7.3).

FULL PRESCRIBING INFORMATION

1 INDICATIONS AND USAGE

Sodium polystyrene sulfonate for suspension is indicated for the treatment of hyperkalemia.

Limitation of Use:

Sodium polystyrene sulfonate for suspension should not be used as an emergency treatment for life-threatening hyperkalemia because of its delayed onset of action [see Clinical Pharmacology (12.2)]

2 DOSAGE AND ADMINISTRATION

2.1 General Information

Administer sodium polystyrene sulfonate at least 3 hours before or 3 hours after other oral medications. Patients with gastroparesis may require a 6 hour separation [see Warnings and Precautions(5.5) and Drug Interaction(7)]

2.2 Recommended Dosage

The intensity and duration of therapy depend upon the severity and resistance of hyperkalemia.

Oral

The average total daily adult dose of sodium polystyrene sulfonate is 15 g to 60 g, administered as a 15-g dose (four level teaspoons), one to four times daily.

Rectal

The average adult dose is 30 g to 50 g every six hours.

2.3 Preparation and Administration

Prepare suspension fresh and use within 24 hours.

Do not heat sodium polystyrene sulfonate as it could alter the exchange properties of the resin.

One level teaspoon contains approximately 3.5 g of sodium polystyrene sulfonate and 15 mEq of sodium.

Oral Suspension

Suspend each dose in a small quantity of water or syrup, approximately 3 to 4 mL of liquid per gram of resin. Administer with patient in an upright position [see Warnings and Precautions (5.4)].

Enema

After an initial cleansing enema, insert a soft, large size (French 28) rubber tube into the rectum for a distance of about 20 cm, with the tip well into the sigmoid colon, and tape in place.

Administer as a warm (body temperature) emulsion in 100 mL of aqueous vehicle and flush with 50 to 100 ml of fluid. A somewhat thicker suspension may be used, but do not form a paste.

Agitate the emulsion gently during administration. The resin should be retained for as long as possible and follow by a cleansing enema with a nonsodium containing solution. Ensure an adequate volume of cleansing solution (up to 2 liters) is utilized.

3 DOSAGE FORMS AND STRENGTHS

Sodium polystyrene sulfonate for suspension is a golden brown, finely ground powder and is available in 454 g jars and 15 g bottles.

4 CONTRAINDICATIONS

Sodium polystyrene sulfonate is contraindicated in patients with the following conditions:

- Hypersensitivity to polystyrene sulfonate resins
- Obstructive bowel disease
- Neonates with reduced gut motility

5 WARNINGS AND PRECAUTIONS

5.1 Intestinal Necrosis

Cases of intestinal necrosis, some fatal, and other serious gastrointestinal adverse events (bleeding, ischemic colitis, perforation) have been reported in association with sodium polystyrene sulfonate use. The majority of these cases reported the concomitant use of sorbitol. Risk factors for gastrointestinal adverse events were present in many of the cases including prematurity, history of intestinal disease or surgery, hypovolemia, and renal insufficiency and failure. Concomitant administration of sorbitol is not recommended.

- Use only in patients who have normal bowel function. Avoid use in patients who have not had a bowel movement post-surgery.
- Avoid use in patients who are at risk for developing constipation or impaction (including those with history of impaction, chronic constipation, inflammatory bowel disease, ischemic colitis, vascular intestinal atherosclerosis, previous bowel resection, or bowel obstruction). Discontinue use in patients who develop constipation.

5.2 Electrolyte Disturbances

Monitor serum potassium during therapy because severe hypokalemia may occur.

Sodium polystyrene sulfonate is not totally selective for potassium, and small amounts of other cations such as magnesium and calcium can also be lost during treatment. Monitor calcium and magnesium in patients receiving sodium polystyrene sulfonate.

5.3 Fluid Overload in Patients Sensitive to High Sodium Intake

Each 15 g dose of sodium polystyrene sulfonate contains 1500 mg (60 mEq) of sodium. Monitor patients who are sensitive to sodium intake (heart failure, hypertension, edema) for signs of fluid overload. Adjustment of other sources of sodium may be required.

5.4 Risk of Aspiration

Cases of acute bronchitis or bronchopneumonia caused by inhalation of sodium polystyrene sulfonate particles have been reported. Patients with impaired gag reflex, altered level of consciousness, or patients prone to regurgitation may be at increased risk. Administer sodium polystyrene sulfonate with the patient in an upright position.

5.5 Binding to Other Orally Administered Medications

Sodium polystyrene sulfonate may bind orally administered medications, which could decrease their gastrointestinal absorption and lead to reduced efficacy. Administer other oral medications at least 3 hours before or 3 hours after sodium polystyrene sulfonate. Patients with gastroparesis may require a 6 hour separation. [see Dosage and Administration (2.1) and Drug Interactions (7)].

6 ADVERSE REACTIONS

The following adverse reactions are discussed elsewhere in the labeling:

- Intestinal Necrosis [see Warnings and Precautions (5.1)]
- Electrolyte Disturbances [see Warnings and Precautions (5.2, 5.3)]
- Aspiration [see Warnings and Precautions (5.4)]

The following adverse reactions have been identified during post-approval use of sodium polystyrene sulfonate. Because these reactions are reported voluntarily from a population of uncertain size, it is not always possible to estimate their frequency reliably or establish a causal relationship to drug exposure.

Gastrointestinal: anorexia, constipation, diarrhea, fecal impaction, gastrointestinal concretions (bezoars), ischemic colitis, nausea, ulcerations, vomiting, gastric irritation, intestinal obstruction (due to concentration of aluminium hydroxide)

Metabolic: systemic alkalosis

7 DRUG INTERACTIONS

7.1 General Interactions

No formal drug interaction studies have been conducted in humans.

Sodium polystyrene sulfonate has the potential to bind other drugs. In in vitro binding studies, sodium polystyrene sulfonate was shown to significantly bind the oral medications (n=6) that were tested. Decreased absorption of lithium and thyroxine have also been reported with co-administration of sodium polystyrene sulfonate. Binding of sodium polystyrene sulfonate to other oral medications could cause decreased gastrointestinal absorption and loss of efficacy when taken close to the time sodium polystyrene sulfonate is administered. Administer sodium polystyrene sulfonate at least 3 hours before or 3 hours after other oral medications. Patients with gastroparesis may require a 6 hour separation. Monitor for clinical response and/or blood levels where possible.

7.2 Cation-Donating Antacids

The simultaneous oral administration of sodium polystyrene sulfonate with nonabsorbable cation-donating antacids and laxatives may reduce the resin's potassium exchange capability and increase the risk of systemic alkalosis.

7.3 Sorbitol

Sorbitol may contribute to the risk of intestinal necrosis [see Warnings and Precautions (5.1)] and concomitant use is not recommended.

8 USE IN SPECIFIC POPULATIONS

8.1 Pregnancy

Risk Summary

Sodium polystyrene sulfonate is not absorbed systemically following oral or rectal administration and maternal use is not expected to result in fetal risk.

8.2 Lactation

Risk Summary

Sodium polystyrene sulfonate is not absorbed systemically by the mother, so breastfeeding is not expected to result in risk to the infant.

8.4 Pediatric Use

Studies of safety and efficacy have not been conducted in pediatric patients.

In pediatric patients, as in adults, sodium polystyrene sulfonate is expected to bind potassium at the practical exchange ratio of 1mEq potassium per 1 gram of resin.

In neonates, sodium polystyrene sulfonate should not be given by the oral route. In both children and neonates, excessive dosage or inadequate dilution could result in impaction of the resin. Premature infants or low birth weight infants may have an increased risk for gastrointestinal adverse effects with sodium polystyrene sulfonate use [see Warnings and Precautions (5.4)].

10 OVERDOSAGE

Overdosage may result in electrolyte disturbances including hypokalemia, hypocalcemia, and hypomagnesemia. Appropriate measures should be taken to correct serum electrolytes (potassium, calcium, magnesium), and the resin should be removed from the alimentary tract by appropriate use of laxatives or enemas.

11 DESCRIPTION

Sodium polystyrene sulfonate is a benzene, diethenyl- polymer, with ethenylbenzene,
sulfonated, sodium salt and has the following structural formula:

n

The drug is a golden brown finely ground, powdered form of sodium polystyrene sulfonate, a cation-exchange resin prepared in the sodium phase with an in vitro exchange capacity of approximately 3.1 mEq (in vivo approximately 1 mEq) of potassium per gram. The sodium content is approximately 100 mg (4.1 mEq) per gram of the drug. It can be administered orally or in an enema.

One gram of sodium polystyrene sulfonate contains 4.1 mEq of sodium.

12 CLINICAL PHARMACOLOGY

12.1 Mechanism of Action

Sodium polystyrene sulfonate is a non-absorbed, cation exchange polymer that contains a sodium counterion.

Sodium polystyrene sulfonate increases fecal potassium excretion through binding of potassium in the lumen of the gastrointestinal tract. Binding of potassium reduces the concentration of free potassium in the gastrointestinal lumen, resulting in a reduction of serum potassium levels. The practical exchange ratio is 1 mEq K per 1 gram of resin.

As the resin passes along the intestine or is retained in the colon after administration by enema, the sodium ions are partially released and are replaced by potassium ions. This action occurs primarily in the large intestine, which excretes potassium ions to a greater degree than does the small intestine. The efficiency of this process is limited and unpredictably variable.

12.2 Pharmacodynamics

The effective lowering of serum potassium with sodium polystyrene sulfonate may take hours to days.

12.3 Pharmacokinetics

The in vivo efficiency of sodium-potassium exchange resins is approximately 33 percent; hence, about one third of the resin's actual sodium content is delivered to the body.

Sodium polystyrene sulfonate is not absorbed systemically.

Drug Interactions

In vitro binding studies showed that sodium polystyrene sulfonate bound significantly to the following tested drugs – warfarin, metoprolol, phenytoin, furosemide, amlodipine and amoxicillin.

13 NONCLINICAL TOXICOLOGY

13.1 Carcinogenesis, Mutagenesis, Impairment of Fertility

Studies have not been performed.

16 HOW SUPPLIED/STORAGE AND HANDLING

Sodium polystyrene sulfonate for suspension is available as a golden brown, finely ground powder in bottles of 15 g.

NDC: 71335-2855-1: 15 g in a Bottle

Store at 25°C (77°F); excursions permitted to 15°-30°C (59°-86°F) [see USP Controlled Room Temperature]

Repackaged/Relabeled by:
Bryant Ranch Prepack, Inc.
Burbank, CA 91504

17 PATIENT COUNSELING INFORMATION

Drug Interactions

Advise patients who are taking other oral medication to separate the dosing of sodium polystyrene sulfonate by at least 3 hours (before or after) [see Dosage and Administration (2.1), Warnings and Precautions (5.5), and Drug Interactions (7.1)]

Rx Only

Manufactured & Distributed by:
Sunrise Pharmaceutical, Inc.
Rahway, NJ 07065

Revised August 2022
5368/00

PACKAGE LABEL

Sodium Polystyrene Sulfonate Powder #15